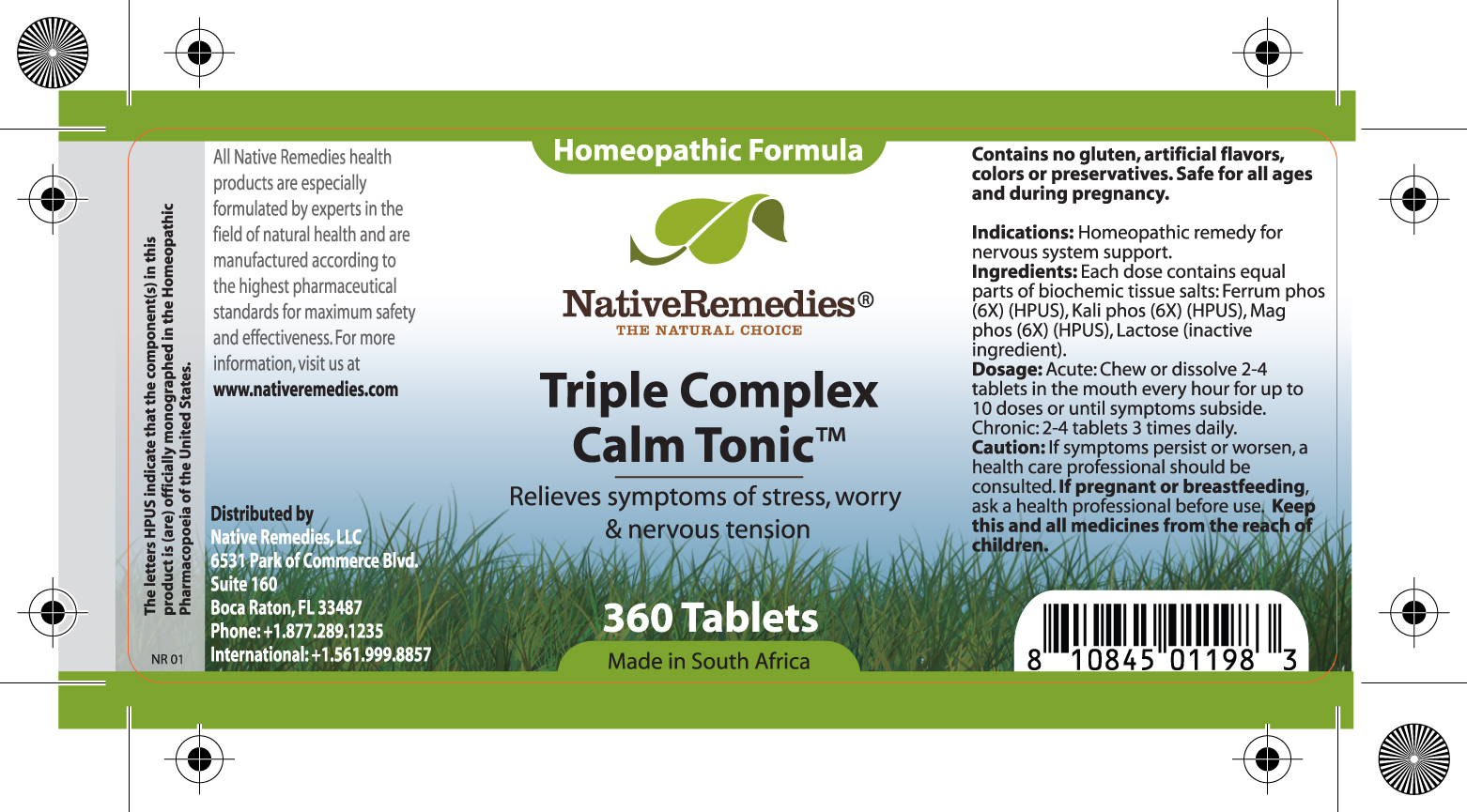 DRUG LABEL: Triple Complex Calm Tonic
NDC: 68647-207 | Form: TABLET
Manufacturer: Feelgood Health
Category: homeopathic | Type: HUMAN OTC DRUG LABEL
Date: 20110620

ACTIVE INGREDIENTS: FERRUM PHOSPHORICUM 6 [hp_X]/1 1; POTASSIUM PHOSPHATE, DIBASIC 6 [hp_X]/1 1; MAGNESIUM PHOSPHATE 6 [hp_X]/1 1
INACTIVE INGREDIENTS: LACTOSE

TRIPLE COMPLEX CALM TONIC

ACTIVE INGREDIENT

Ingredients: Each dose contains equal parts of biochemic tissue salts: Ferrum phos (6X) (HPUS), Kali phos (6X) (HPUS), Mag phos (6X) (HPUS)

PURPOSE

Relieves symptoms of stress, worry and nervous tension

KEEP OUT OF REACH OF CHILDREN

Keep this and all medicines from the reach of children.

Indications: Homeopathic remedy for nervous system support.

WARNINGS

Caution: If symptoms persist or worsen, a health care professional should be consulted

If pregnant or breastfeeding, ask a health professional before use.

Contains no gluten, artificial flavors, colors or preservatives

Safe for all ages and during pregnancy.

DOSAGE AND ADMINISTRATION

Dosage: Acute: Chew or dissolve 2-4 tablets in the mouth every hour for up to 10 doses or until symptoms subside.

Chronic: 2-4 tablets 3 times daily.

Lactose (inactive ingredient).

KEEP OUT OF REACH OF CHILDREN

Keep this and all medicines from the reach of children.

PATIENT COUNSELING INFORMATION

All Native Remedies health products are especially formulated by experts in the field of natural health and are manufactured according to the highest pharmaceutical standards for maximum safety and effectiveness. For more information, visit us at www.nativeremedies.com

Distributed by

Native Remedies, LLC

6531 Park of Commerce Blvd.

Suite 160

Boca Raton, FL 33487

Phone: 1.877.289.1235

International: + 1.561.999.8857

The letters HPUS indicate that the component(s) in this product is (are) officially monographed in the Homeopathic Pharmacopoeia of the United States.